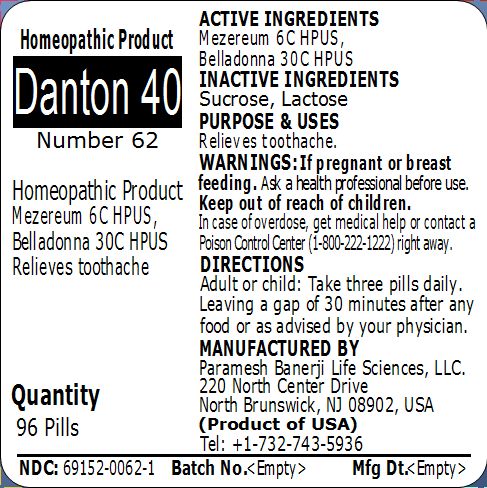 DRUG LABEL: Danton 40 (Number 62)
NDC: 69152-0062 | Form: PELLET
Manufacturer: Paramesh Banerji Life Sciences LLC
Category: homeopathic | Type: HUMAN OTC DRUG LABEL
Date: 20150307

ACTIVE INGREDIENTS: DAPHNE MEZEREUM BARK 6 [hp_C]/1 1; ATROPA BELLADONNA 30 [hp_C]/1 1
INACTIVE INGREDIENTS: LACTOSE; SUCROSE

Active Ingredients

Mezereum 6C HPUS, Belladonna 30C HPUS

Inactive Ingredients

Sucrose, Lactose

Purpose

Relieves toothache

Uses

Relieves toothache

Warnings

If pregnant or breast feeding ask a health professional before use.

Keep out of reach of children. In case of overdose, get medical help or contact a Poison Control Center (1-800-222-1222) right away.

Direction

Adult or child: Take three pills daily. Leaving a gap of 30 minutes after any food or as advised by your physician.

Manufactured by

Paramesh Banerji Life Sciences, LLC

220 North Center Drive

North Brunswick, NJ 08902, USA

Product of USA

Tel: +1-732-743-5936

Principal Display Panel

Homeopathic Product

Danton 40

Number 62

Homeopathic Product

Mezereum 6C HPUS, Belladonna 30C HPUS

Relieves toothache

Quantity

96 Pills